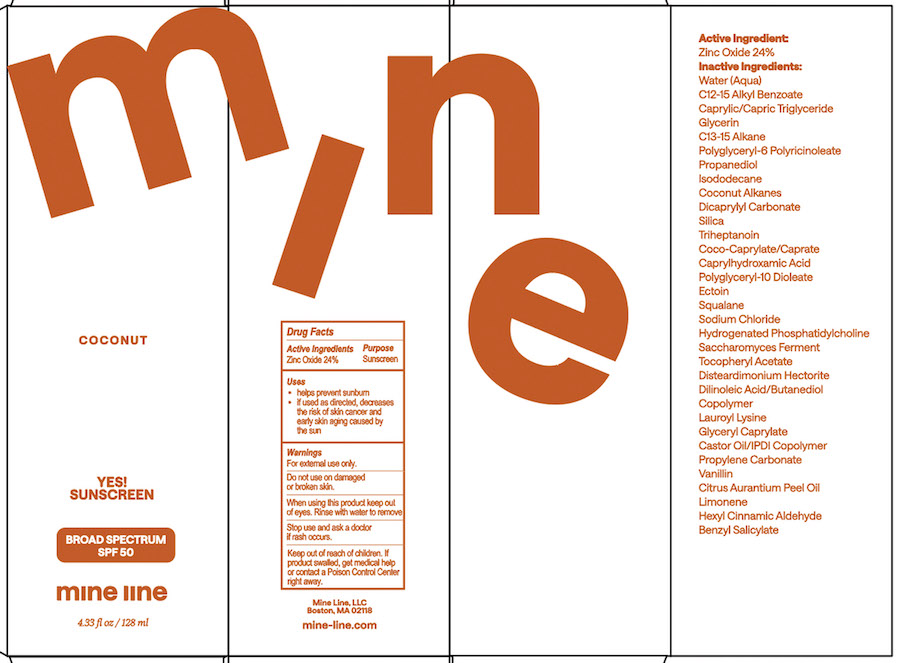 DRUG LABEL: Mine Line Coconut Sunscreen SPF 50
NDC: 68062-7301 | Form: LOTION
Manufacturer: Spa de Soleil
Category: otc | Type: HUMAN OTC DRUG LABEL
Date: 20251229

ACTIVE INGREDIENTS: ZINC OXIDE 31 mg/128 mL
INACTIVE INGREDIENTS: DILINOLEIC ACID/BUTANEDIOL COPOLYMER; LAUROYL LYSINE; WATER; C12-15 ALKYL BENZOATE; CAPRYLIC/CAPRIC TRIGLYCERIDE; GLYCERIN; C13-15 ALKANE; POLYGLYCERYL-6 POLYRICINOLEATE; PROPANEDIOL; ISODODECANE; COCONUT ALKANES; DICAPRYLYL CARBONATE; TRIHEPTANOIN; COCO-CAPRYLATE/CAPRATE; CAPRYLHYDROXAMIC ACID; POLYGLYCERYL-10 DIOLEATE; ECTOIN; SQUALANE; SODIUM CHLORIDE; HYDROGENATED SOYBEAN PHOSPHATIDYLCHOLINE; CASTOR OIL/IPDI COPOLYMER; .ALPHA.-TOCOPHEROL ACETATE, DL-; GLYCERYL CAPRYLATE; PROPYLENE CARBONATE; DISTEARDIMONIUM HECTORITE

Mine Line Coconut Sunscreen SPF 50

Active Ingredients

Zinc Oxide 24%

Purpose

Sunscreen

Warnings

WarningsWhen using this product

- keep out of the eye area
- rinse with water to remove
- stop use and ask a doctor if rash or irritation develops
- for external use onlyl
- keep out of reach of children

Keep out of reach of children.

Directions

Apply thin layer over clean, dry skin. Massage well. Allow 15 minutes of complete penetration before sun exposure. Reapply every 1-2 hours & after swimming or sweating. Protect the product in this container from excessive heat.

Uses
Provides high protection against sunburn.

Inactive Ingredients

Water, C12-15 Alkyl Benzoate, Caprylic/Capric Triglyceride, Glycerin, C13-15 Alkane, Polyglyceryl-6 Polyricinoleate, Propanediol, Isododecane, Coconut Alkanes, Dicaprylyl Carbonate, Triheptanoin, Coco-Caprylate/Caprate, Caprylhydroxamic Acid, Polyglyceryl-10 Dioleate, Ectoin, Squalane, Sodium Chloride, Hydrogenated Phosphatidylcholine, Saccharomyces Ferment, Tocopheryl Acetate, Disteardimonium Hectorite, Dilinoleic Acid/Butanediol Copolymer, Lauroyl Lysine, Glyceryl Caprylate, Castor Oil/IPDI Copolymer, Propylene Carbonate